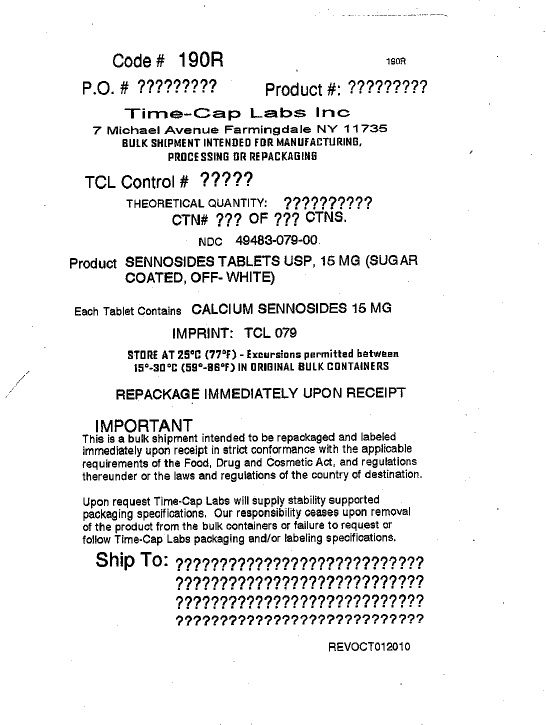 DRUG LABEL: SENNOSIDES
NDC: 49483-079 | Form: TABLET, SUGAR COATED
Manufacturer: TIME CAP LABORATORIES, INC
Category: otc | Type: HUMAN OTC DRUG LABEL
Date: 20250207

ACTIVE INGREDIENTS: SENNOSIDES A AND B 15 mg/1 1
INACTIVE INGREDIENTS: FD&C RED NO. 40; FD&C YELLOW NO. 6; KAOLIN; MAGNESIUM STEARATE; MALTODEXTRIN; MICROCRYSTALLINE CELLULOSE; POLYETHYLENE GLYCOL, UNSPECIFIED; RAW SUGAR; TALC; ACACIA; POVIDONE; SHELLAC; TITANIUM DIOXIDE; FERRIC OXIDE YELLOW; CALCIUM SULFATE ANHYDROUS; CARNAUBA WAX; STARCH, CORN; CROSCARMELLOSE SODIUM; FERROSOFERRIC OXIDE; DIBASIC CALCIUM PHOSPHATE DIHYDRATE; FD&C BLUE NO. 1

190R Sennosides tablets USP 15 mg sugar coated off-white

ACTIVE INGREDIENT

Each Tablet contains:

Sennosides 15 mg

INACTIVE INGREDIENT

INACTIVE INGREDIENTS:acacia, calcium sulfate anhydrous, carnauba wax, corn starch, croscarmellose sodium, dibasic calcium phosphate dihydrate, FD&C blue#1, FD&C Red#40, FD&C Yellow#6, iron oxide, iron oxide black, iron oxide yellow, Kaolin, magnesium stearate, maltodextrin, microcrystalline cellulose, polyethylene glycol(PEG 400), povidone, Shellac, Sugar, Talc, Titanium dioxide

PURPOSE

stool softner, laxative

Directions:

Take preferably at bedtime or as directed by a doctor. If you do not have a comfortable bowel movement by the second day, increase dose by one tablet (not to exceed maximum dosage) or decrease dose until you are comfortable.

Adults and children 12 years and over - starting dosage: 2 tablets once a day maximum dosage: 4 tablets twice a day

Children 6 to under 12 years - starting dosage: 1 tablet once a day maximum dosage: 2 tablets twice a day

Children 6 to under 12 years - starting dosage: 1/2 tablet once a day maximum dosage: 1 tablet twice a day

Children under 2 years - Ask a doctor

Uses:

Relieves occasional constipation (irregularity); generally causes bowel movement in 6-12 hours

WARNINGS:

Do not use this product
If you are presently taking mineral oil, unless directed by a doctor
Laxative products for longer than 1 week unless directed by a doctor

KEEP OUT OF REACH OF CHILDREN

Keep out of the reach of children. Incase of overdose, get medical help or contact a Poison Control Center right away.

PACKAGE LABEL

NDC: 49483-079-00